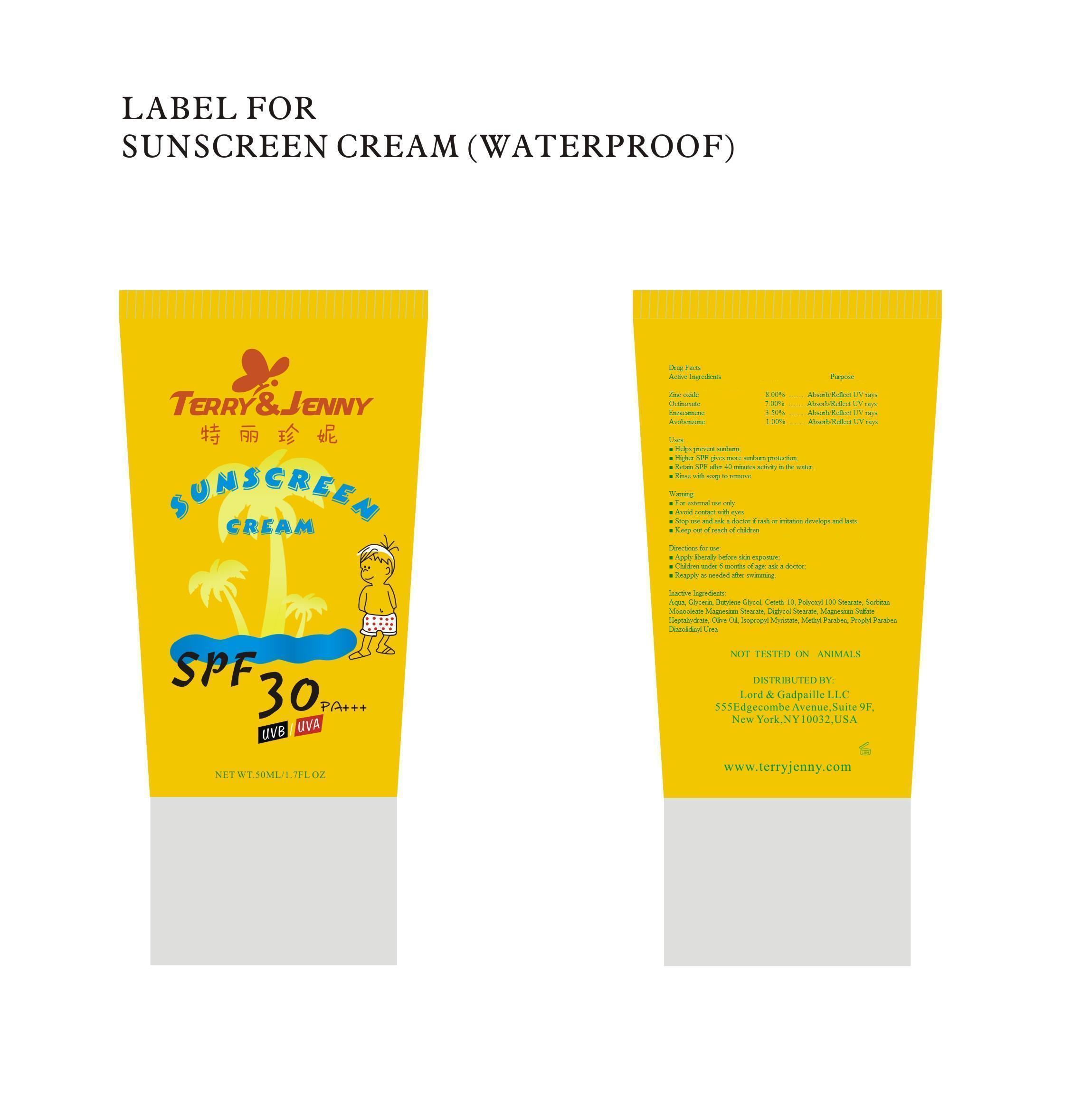 DRUG LABEL: Correway Sunscreen (Waterproof)
NDC: 50600-003 | Form: CREAM
Manufacturer: Ningbo Correway Cosmetics Co., Ltd.
Category: otc | Type: HUMAN OTC DRUG LABEL
Date: 20100423

ACTIVE INGREDIENTS: Zinc Oxide 80 mg/1 g; Octinoxate 70 mg/1 g; Enzacamene 35 mg/1 g; Avobenzone 10 mg/1 g
INACTIVE INGREDIENTS: Water; Glycerin; Butylene Glycol; Ceteth-10; Polyoxyl 100 Stearate; Sorbitan Monooleate; Magnesium Stearate; Diglycol Stearate; Magnesium Sulfate Heptahydrate; Olive Oil; Isopropyl Myristate; Methylparaben; Propylparaben; Diazolidinylurea

Drug Facts

ACTIVE INGREDIENT

Zinc Oxide, Octinoxate, Enzacamene, Avobenzone

Ask Doctor

Stop use and ask a doctor if rash or irritation develops and lasts.
Children under 6 months of age: ask a doctor;

Warning

For external use only;
Avoid contact with eyes;
Stop use and ask a doctor if rash or irritation develops and lasts;
Keep out of reach of children.

Keep out of reach of children

PURPOSE

Helps prevent sunburn;
Higher SPF gives more sunburn protection;
Retain SPF after 40 minutes activity in the water;
Rinse with soap to remove.

Stop use and ask a doctor if rash or irritation develops and lasts.

WHEN USING

Apply liberally before skin exposure;
Reapply as needed after swimming.